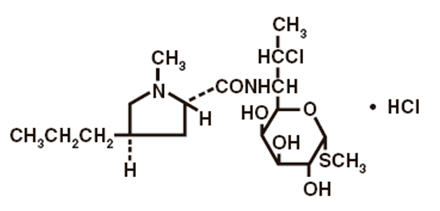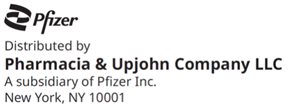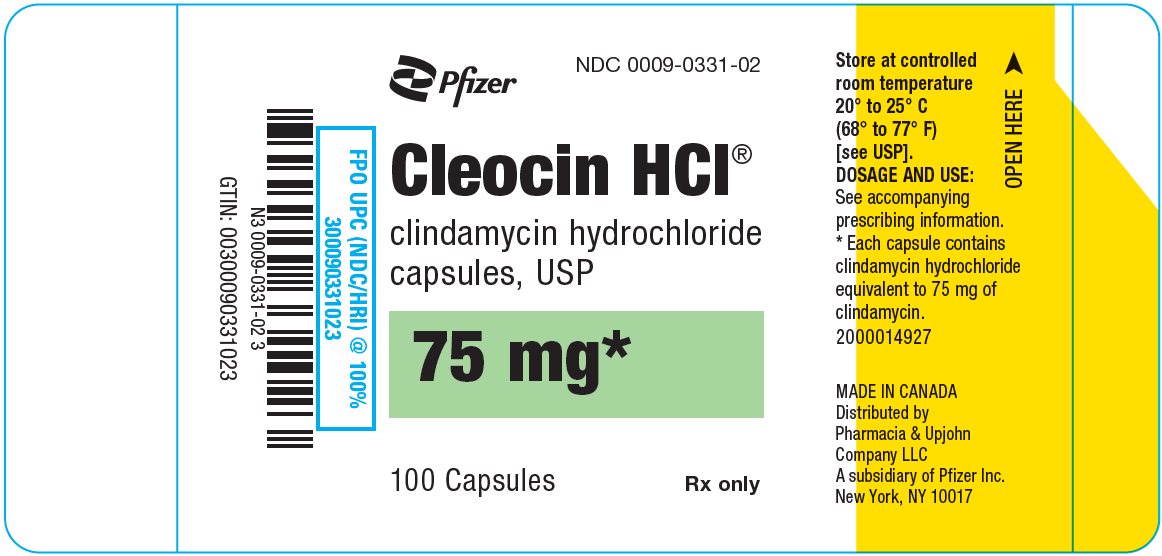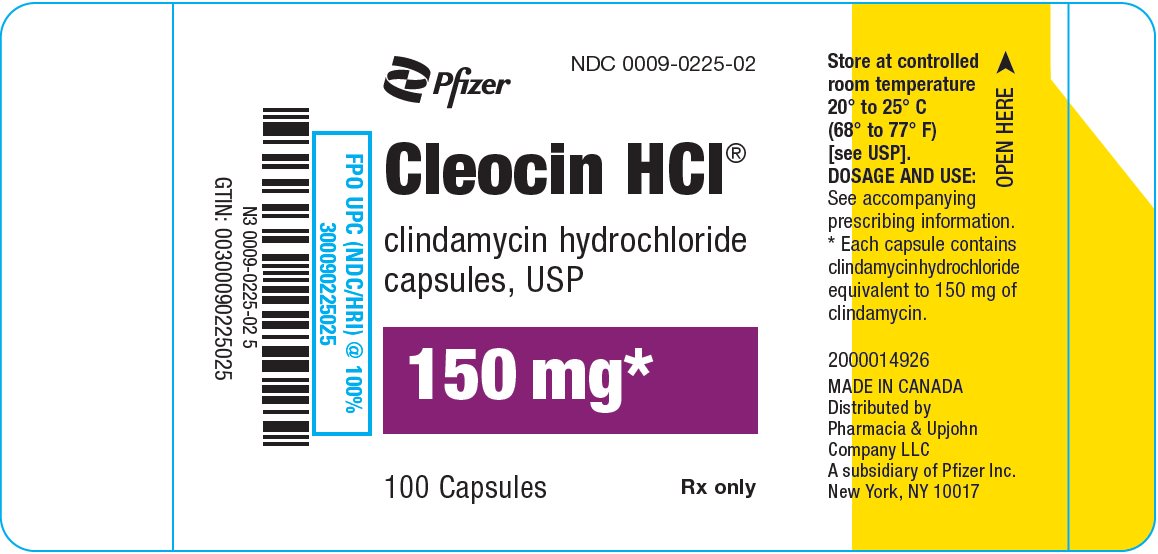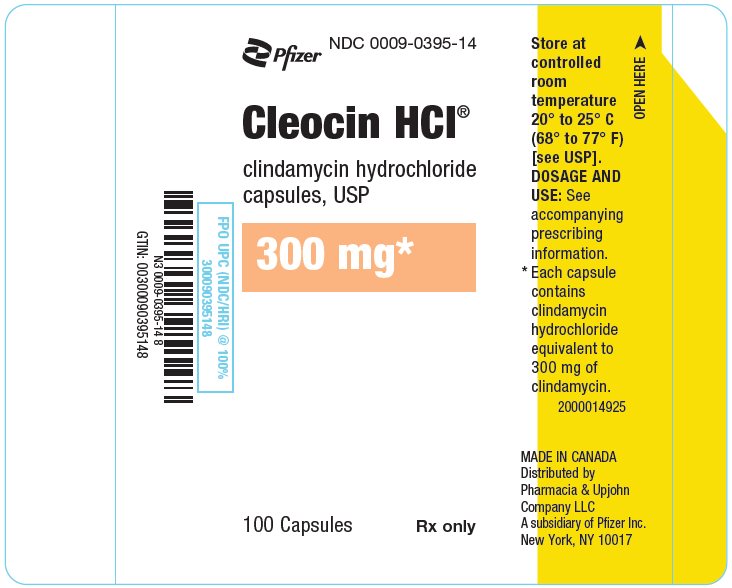 DRUG LABEL: Cleocin Hydrochloride
NDC: 0009-0331 | Form: CAPSULE
Manufacturer: Pharmacia & Upjohn Company LLC
Category: prescription | Type: HUMAN PRESCRIPTION DRUG LABEL
Date: 20251014

ACTIVE INGREDIENTS: CLINDAMYCIN HYDROCHLORIDE 75 mg/1 1
INACTIVE INGREDIENTS: STARCH, CORN; FD&C BLUE NO. 1; FD&C YELLOW NO. 5; GELATIN, UNSPECIFIED; LACTOSE, UNSPECIFIED FORM; MAGNESIUM STEARATE; TALC

CLEOCIN HCl®
clindamycin hydrochloride
capsules, USP

To reduce the development of drug-resistant bacteria and maintain the effectiveness of CLEOCIN HCl and other antibacterial drugs, CLEOCIN HCl should be used only to treat or prevent infections that are proven or strongly suspected to be caused by bacteria.

WARNING

Clostridioides difficile-associated diarrhea (CDAD) has been reported with use of nearly all antibacterial agents, including CLEOCIN HCl and may range in severity from mild diarrhea to fatal colitis. Treatment with antibacterial agents alters the normal flora of the colon, leading to overgrowth of C. difficile.

Because CLEOCIN HCl therapy has been associated with severe colitis which may end fatally, it should be reserved for serious infections where less toxic antimicrobial agents are inappropriate, as described in the INDICATIONS AND USAGE section. It should not be used in patients with nonbacterial infections such as most upper respiratory tract infections.

C. difficile produces toxins A and B, which contribute to the development of CDAD. Hypertoxin producing strains of C. difficile cause increased morbidity and mortality, as these infections can be refractory to antimicrobial therapy and may require colectomy. CDAD must be considered in all patients who present with diarrhea following antibacterial drug use. Careful medical history is necessary since CDAD has been reported to occur over two months after the administration of antibacterial agents.

If CDAD is suspected or confirmed, ongoing antibacterial drug use not directed against C. difficile may need to be discontinued. Appropriate fluid and electrolyte management, protein supplementation, antibacterial drug treatment of C. difficile, and surgical evaluation should be instituted as clinically indicated.

DESCRIPTION

Clindamycin hydrochloride is the hydrated hydrochloride salt of clindamycin. Clindamycin is a semisynthetic antibacterial drug produced by a 7(S)-chloro-substitution of the 7(R)-hydroxyl group of the parent compound lincomycin.

CLEOCIN HCl Capsules contain clindamycin hydrochloride equivalent to 75 mg, 150 mg, or 300 mg of clindamycin.

Inactive ingredients: 75 mg – corn starch, FD&C blue no. 1, FD&C yellow no. 5, gelatin, lactose, magnesium stearate, and talc; 150 mg – corn starch, FD&C blue no. 1, FD&C yellow no. 5, gelatin, lactose, magnesium stearate, talc and titanium dioxide; 300 mg – corn starch, FD&C blue no. 1, gelatin, lactose, magnesium stearate, talc, and titanium dioxide.

The structural formula is represented below:

The chemical name for clindamycin hydrochloride is Methyl 7-chloro-6,7,8-trideoxy-6-(1-methyl-trans-4-propyl-L-2-pyrrolidinecarboxamido)-1-thio-L-threo-α-D-galacto-octopyranoside monohydrochloride.

CLINICAL PHARMACOLOGY

Human Pharmacology

Absorption

Pharmacokinetic studies with a 150 mg oral dose of clindamycin hydrochloride in 24 normal adult volunteers showed that clindamycin was rapidly absorbed after oral administration. An average peak serum concentration of 2.50 mcg/mL was reached in 45 minutes; serum concentrations averaged 1.51 mcg/mL at 3 hours and 0.70 mcg/mL at 6 hours. Absorption of an oral dose is virtually complete (90%), and the concomitant administration of food does not appreciably modify the serum concentrations; serum concentrations have been uniform and predictable from person to person and dose to dose. Pharmacokinetic studies following multiple doses of CLEOCIN HCl for up to 14 days show no evidence of accumulation or altered metabolism of drug. Doses of up to 2 grams of clindamycin per day for 14 days have been well tolerated by healthy volunteers, except that the incidence of gastrointestinal side effects is greater with the higher doses.

Distribution

Concentrations of clindamycin in the serum increased linearly with increased dose. Serum concentrations exceed the MIC (minimum inhibitory concentration) for most indicated organisms for at least six hours following administration of the usually recommended doses. Clindamycin is widely distributed in body fluids and tissues (including bones). No significant concentrations of clindamycin are attained in the cerebrospinal fluid, even in the presence of inflamed meninges.

Metabolism

In vitro studies in human liver and intestinal microsomes indicated that clindamycin is predominantly metabolized by Cytochrome P450 3A4 (CYP3A4), with minor contribution from CYP3A5, to form clindamycin sulfoxide and a minor metabolite, N-desmethylclindamycin.

Excretion

The average biological half-life is 2.4 hours. Approximately 10% of the bioactivity is excreted in the urine and 3.6% in the feces; the remainder is excreted as bioinactive metabolites.

Specific Populations

Patients with Renal/Hepatic Impairment

The elimination half-life of clindamycin is increased slightly in patients with markedly reduced renal or hepatic function. Hemodialysis and peritoneal dialysis are not effective in removing clindamycin from the serum. Dosage schedules do not need to be modified in patients with renal disease.

Geriatric Patients

Pharmacokinetic studies in elderly volunteers (61–79 years) and younger adults (18–39 years) indicate that age alone does not alter clindamycin pharmacokinetics (clearance, elimination half-life, volume of distribution, and area under the serum concentration-time curve) after IV administration of clindamycin phosphate. After oral administration of clindamycin hydrochloride, the average elimination half-life is increased to approximately 4.0 hours (range 3.4–5.1 h) in the elderly compared to 3.2 hours (range 2.1 – 4.2 h) in younger adults. The extent of absorption, however, is not different between age groups and no dosage alteration is necessary for the elderly with normal hepatic function and normal (age-adjusted) renal function^1.

Obese Pediatric Patients Aged 2 to Less than 18 Years and Obese Adults Aged 18 to 20 Years

An analysis of pharmacokinetic data in obese pediatric patients aged 2 to less than 18 years and obese adults aged 18 to 20 years demonstrated that clindamycin clearance and volume of distribution, normalized by total body weight, are comparable regardless of obesity.

Microbiology

Mechanism of Action

Clindamycin inhibits bacterial protein synthesis by binding to the 23S RNA of the 50S subunit of the ribosome. Clindamycin is bacteriostatic.

Resistance

Resistance to clindamycin is most often caused by modification of specific bases of the 23S ribosomal RNA. Cross-resistance between clindamycin and lincomycin is complete. Because the binding sites for these antibacterial drugs overlap, cross-resistance is sometimes observed among lincosamides, macrolides and streptogramin B. Macrolide-inducible resistance to clindamycin occurs in some isolates of macrolide-resistant bacteria. Macrolide-resistant isolates of staphylococci and beta-hemolytic streptococci should be screened for induction of clindamycin resistance using the D-zone test.

Antimicrobial Activity

Clindamycin has been shown to be active against most of the isolates of the following microorganisms, both in vitro and in clinical infections (See INDICATIONS AND USAGE):

Gram-positive bacteria

Staphylococcus aureus (methicillin-susceptible strains)
Streptococcus pneumoniae (penicillin-susceptible strains)
Streptococcus pyogenes

Anaerobic bacteria

Clostridium perfringens
Fusobacterium necrophorum
Fusobacterium nucleatum
Peptostreptococcus anaerobius
Prevotella melaninogenica

The following in vitro data are available, but their clinical significance is unknown. At least 90 percent of the following bacteria exhibit an in vitro minimum inhibitory concentration (MIC) less than or equal to the susceptible breakpoint for clindamycin against isolates of a similar genus or organism group. However, the efficacy of clindamycin in treating clinical infections due to these bacteria has not been established in adequate and well-controlled clinical trials.

Gram-positive bacteria

Staphylococcus epidermidis (methicillin-susceptible strains)
Streptococcus agalactiae
Streptococcus anginosus
Streptococcus mitis
Streptococcus oralis

Anaerobic bacteria

Actinomyces israelii
Clostridium clostridioforme
Eggerthella lenta
Finegoldia (Peptostreptococcus) magna
Micromonas (Peptostreptococcus) micros
Prevotella bivia
Prevotella intermedia
Cutibacterium acnes

Susceptibility Testing

For specific information regarding susceptibility test interpretive criteria and associated test methods and quality control standards recognized by FDA for this drug, please see: https://www.fda.gov/STIC.

INDICATIONS AND USAGE

Clindamycin is indicated in the treatment of serious infections caused by susceptible anaerobic bacteria.

Clindamycin is also indicated in the treatment of serious infections due to susceptible strains of streptococci, pneumococci, and staphylococci. Its use should be reserved for penicillin-allergic patients or other patients for whom, in the judgment of the physician, a penicillin is inappropriate. Because of the risk of colitis, as described in the BOXED WARNING, before selecting clindamycin, the physician should consider the nature of the infection and the suitability of less toxic alternatives (e.g., erythromycin).

Anaerobes: Serious respiratory tract infections such as empyema, anaerobic pneumonitis, and lung abscess; serious skin and soft tissue infections; septicemia; intra-abdominal infections such as peritonitis and intra-abdominal abscess (typically resulting from anaerobic organisms resident in the normal gastrointestinal tract); infections of the female pelvis and genital tract such as endometritis, nongonococcal tubo-ovarian abscess, pelvic cellulitis, and postsurgical vaginal cuff infection.

Streptococci: Serious respiratory tract infections; serious skin and soft tissue infections.

Staphylococci: Serious respiratory tract infections; serious skin and soft tissue infections.

Pneumococci: Serious respiratory tract infections.

Bacteriologic studies should be performed to determine the causative organisms and their susceptibility to clindamycin.

To reduce the development of drug-resistant bacteria and maintain the effectiveness of CLEOCIN HCl and other antibacterial drugs, CLEOCIN HCl should be used only to treat or prevent infections that are proven or strongly suspected to be caused by susceptible bacteria. When culture and susceptibility information are available, they should be considered in selecting or modifying antibacterial therapy. In the absence of such data, local epidemiology and susceptibility patterns may contribute to the empiric selection of therapy.

CONTRAINDICATIONS

CLEOCIN HCl is contraindicated in individuals with a history of hypersensitivity to preparations containing clindamycin or lincomycin.

WARNINGS

See BOXED WARNING

Clostridioides difficile-associated diarrhea (CDAD) has been reported with use of nearly all antibacterial agents, including CLEOCIN HCl, and may range in severity from mild diarrhea to fatal colitis. Treatment with antibacterial agents alters the normal flora of the colon, leading to overgrowth of C. difficile.

C. difficile produces toxins A and B, which contribute to the development of CDAD. Hypertoxin producing strains of C. difficile cause increased morbidity and mortality, as these infections can be refractory to antimicrobial therapy and may require colectomy. CDAD must be considered in all patients who present with diarrhea following antibacterial drug use. Careful medical history is necessary since CDAD has been reported to occur over two months after the administration of antibacterial agents.

If CDAD is suspected or confirmed, ongoing antibacterial drug use not directed against C. difficile may need to be discontinued. Appropriate fluid and electrolyte management, protein supplementation, antibacterial drug treatment of C. difficile, and surgical evaluation should be instituted as clinically indicated.

Anaphylactic and Severe Hypersensitivity Reactions

Anaphylactic shock and anaphylactic reactions have been reported (See ADVERSE REACTIONS).

Severe hypersensitivity reactions, including severe skin reactions such as toxic epidermal necrolysis (TEN), drug reaction with eosinophilia and systemic symptoms (DRESS), Stevens-Johnson syndrome (SJS), and Kounis syndrome, some with fatal outcome, have been reported (See ADVERSE REACTIONS).

In case of such an anaphylactic or severe hypersensitivity reaction, discontinue treatment permanently and institute appropriate therapy.

A careful inquiry should be made concerning previous sensitivities to drugs and other allergens.

Nephrotoxicity

Clindamycin is potentially nephrotoxic and cases with acute kidney injury have been reported. Consider monitoring of renal function particularly in patients with pre-existing renal dysfunction or those taking concomitant nephrotoxic drugs. In case of acute kidney injury, discontinue CLEOCIN HCl when no other etiology is identified.

Usage in Meningitis

Since clindamycin does not diffuse adequately into the cerebrospinal fluid, the drug should not be used in the treatment of meningitis.

PRECAUTIONS

General

Review of experience to date suggests that a subgroup of older patients with associated severe illness may tolerate diarrhea less well. When clindamycin is indicated in these patients, they should be carefully monitored for change in bowel frequency.

CLEOCIN HCl should be prescribed with caution in individuals with a history of gastrointestinal disease, particularly colitis.

CLEOCIN HCl should be prescribed with caution in atopic individuals.

Indicated surgical procedures should be performed in conjunction with antibacterial drug therapy.

The use of CLEOCIN HCl occasionally results in overgrowth of nonsusceptible organisms—particularly yeasts. Should superinfections occur, appropriate measures should be taken as indicated by the clinical situation.

Clindamycin dosage modification is not necessary in patients with renal disease. In patients with moderate to severe liver disease, prolongation of clindamycin half-life has been found. However, it was postulated from studies that when given every eight hours, accumulation should rarely occur. Therefore, dosage modification in patients with liver disease may not be necessary. However, periodic liver enzyme determinations should be made when treating patients with severe liver disease.

The 75 mg and 150 mg capsules contain FD&C yellow no. 5 (tartrazine), which may cause allergic-type reactions (including bronchial asthma) in certain susceptible individuals. Although the overall incidence of FD&C yellow no. 5 (tartrazine) sensitivity in the general population is low, it is frequently seen in patients who also have aspirin hypersensitivity.

Prescribing CLEOCIN HCl in the absence of a proven or strongly suspected bacterial infection or a prophylactic indication is unlikely to provide benefit to the patient and increases the risk of the development of drug-resistant bacteria.

Due to the risk of esophagitis and esophageal ulcer, it is important to ensure adherence with administration guidance (See DOSAGE AND ADMINISTRATION and ADVERSE REACTIONS).

Information for Patients

Patients should be counseled that antibacterial drugs, including CLEOCIN HCl, should only be used to treat bacterial infections. They do not treat viral infections (e.g., the common cold). When CLEOCIN HCl is prescribed to treat a bacterial infection, patients should be told that although it is common to feel better early in the course of therapy, the medication should be taken exactly as directed. Skipping doses or not completing the full course of therapy may (1) decrease the effectiveness of the immediate treatment and (2) increase the likelihood that bacteria will develop resistance and will not be treatable by CLEOCIN HCl or other antibacterial drugs in the future.

Diarrhea is a common problem caused by antibacterial drugs which usually ends when the antibacterial drug is discontinued. Sometimes after starting treatment with antibacterial drugs, patients can develop watery and bloody stools (with or without stomach cramps and fever) even as late as two or more months after having taken the last dose of the antibacterial drug. If this occurs, patients should contact their physician as soon as possible.

Advise patients that due to the risk of esophagitis and esophageal ulcer, it is important to adhere to the administration guidance for CLEOCIN HCl Capsules (See DOSAGE AND ADMINISTRATION and ADVERSE REACTIONS).

Laboratory Tests

During prolonged therapy, periodic liver and kidney function tests and blood counts should be performed.

Drug Interactions

Clindamycin has been shown to have neuromuscular blocking properties that may enhance the action of other neuromuscular blocking agents. Therefore, it should be used with caution in patients receiving such agents.

Clindamycin is metabolized predominantly by CYP3A4, and to a lesser extent by CYP3A5, to the major metabolite clindamycin sulfoxide and minor metabolite N-desmethylclindamycin. Therefore, inhibitors of CYP3A4 and CYP3A5 may increase plasma concentrations of clindamycin and inducers of these isoenzymes may reduce plasma concentrations of clindamycin. In the presence of strong CYP3A4 inhibitors, monitor for adverse reactions. In the presence of strong CYP3A4 inducers such as rifampicin, monitor for loss of effectiveness.

In vitro studies indicate that clindamycin does not inhibit CYP1A2, CYP2C9, CYP2C19, CYP2E1 or CYP2D6 and only moderately inhibits CYP3A4.

Carcinogenesis, Mutagenesis, Impairment of Fertility

Long-term studies in animals have not been performed with clindamycin to evaluate carcinogenic potential. Genotoxicity tests performed included a rat micronucleus test and an Ames Salmonella reversion test. Both tests were negative.

Fertility studies in rats treated orally with up to 300 mg/kg/day (approximately 1.6 times the highest recommended adult human dose based on mg/m^2) revealed no effects on fertility or mating ability.

Pregnancy:

Teratogenic effects

In clinical trials with pregnant women, the systemic administration of clindamycin during the second and third trimesters, has not been associated with an increased frequency of congenital abnormalities.

Clindamycin should be used during the first trimester of pregnancy only if clearly needed. There are no adequate and well-controlled studies in pregnant women during the first trimester of pregnancy. Because animal reproduction studies are not always predictive of the human response, this drug should be used during pregnancy only if clearly needed.

Reproduction studies performed in rats and mice using oral doses of clindamycin up to 600 mg/kg/day (3.2 and 1.6 times the highest recommended adult human dose based on mg/m^2, respectively) or subcutaneous doses of clindamycin up to 250 mg/kg/day (1.3 and 0.7 times the highest recommended adult human dose based on mg/m^2, respectively) revealed no evidence of teratogenicity.

Nursing Mothers

Limited published data based on breast milk sampling reports that clindamycin appears in human breast milk in the range of less than 0.5 to 3.8 mcg/mL. Clindamycin has the potential to cause adverse effects on the breast-fed infant's gastrointestinal flora. If oral or intravenous clindamycin is required by a nursing mother, it is not a reason to discontinue breastfeeding, but an alternate drug may be preferred. Monitor the breast-fed infant for possible adverse effects on the gastrointestinal flora, such as diarrhea, candidiasis (thrush, diaper rash) or rarely, blood in the stool indicating possible antibacterial drug-associated colitis.

The developmental and health benefits of breastfeeding should be considered along with the mother's clinical need for clindamycin and any potential adverse effects on the breast-fed child from clindamycin or from the underlying maternal condition.

Pediatric Use

When CLEOCIN HCl is administered to the pediatric population (birth to 16 years), appropriate monitoring of organ system functions is desirable.

Geriatric Use

Clinical studies of clindamycin did not include sufficient numbers of patients age 65 and over to determine whether they respond differently from younger patients. However, other reported clinical experience indicates that antibacterial drug-associated colitis and diarrhea (due to Clostridioides difficile) seen in association with most antibacterial drugs occur more frequently in the elderly (>60 years) and may be more severe. These patients should be carefully monitored for the development of diarrhea.

Pharmacokinetic studies with clindamycin have shown no clinically important differences between young and elderly subjects with normal hepatic function and normal (age-adjusted) renal function after oral or intravenous administration.

ADVERSE REACTIONS

The following reactions have been reported with the use of clindamycin.

Infections and Infestations: Clostridioides difficile colitis

Gastrointestinal: Abdominal pain, pseudomembranous colitis, nausea, vomiting, and diarrhea (See BOXED WARNING). The onset of pseudomembranous colitis symptoms may occur during or after antibacterial treatment (See WARNINGS). Esophagitis and esophageal ulcer have been reported, particularly when taken in a lying position or with a small amount of water. An unpleasant or metallic taste has been reported after oral administration.

Hypersensitivity Reactions: Generalized mild to moderate morbilliform-like (maculopapular) skin rashes are the most frequently reported adverse reactions. Vesiculobullous rashes, as well as urticaria, have been observed during drug therapy. Severe skin reactions such as toxic epidermal necrolysis, some with fatal outcome, have been reported (See WARNINGS). Cases of acute generalized exanthematous pustulosis (AGEP), erythema multiforme, some resembling Stevens-Johnson syndrome, anaphylactic shock, anaphylactic reaction, Kounis syndrome (acute myocardial ischemia with or without myocardial infarction may occur as part of an allergic reaction), cutaneous vasculitis, symmetrical drug-related intertriginous and flexural exanthema, and hypersensitivity have also been reported.

Skin and Mucous Membranes: Pruritus, vaginitis, angioedema and rare instances of exfoliative dermatitis have been reported (See Hypersensitivity Reactions).

Liver: Jaundice and abnormalities in liver function tests have been observed during clindamycin therapy.

Renal: Acute kidney injury (See WARNINGS).

Hematopoietic: Transient neutropenia (leukopenia) and eosinophilia have been reported. Reports of agranulocytosis and thrombocytopenia have been made. No direct etiologic relationship to concurrent clindamycin therapy could be made in any of the foregoing.

Immune System: Drug reaction with eosinophilia and systemic symptoms (DRESS) cases have been reported.

Musculoskeletal: Cases of polyarthritis have been reported.

OVERDOSAGE

Significant mortality was observed in mice at an intravenous dose of 855 mg/kg and in rats at an oral or subcutaneous dose of approximately 2618 mg/kg. In the mice, convulsions and depression were observed.

Hemodialysis and peritoneal dialysis are not effective in removing clindamycin from the serum.

DOSAGE AND ADMINISTRATION

If significant diarrhea occurs during therapy, this antibacterial drug should be discontinued (See BOXED WARNING).

Administer CLEOCIN HCl Capsules with a full glass of water (6 to 8 ounces, approximately 200 to 250 mL) and at least 30 minutes before lying down to reduce the potential for esophageal irritation (See ADVERSE REACTIONS).

Adults: Serious infections – 150 to 300 mg every 6 hours. More severe infections – 300 to 450 mg every 6 hours.

Pediatric Patients (who are able to swallow capsules): Serious infections – 8 to 16 mg/kg/day (4 to 8 mg/lb/day) divided into three or four equal doses. More severe infections – 16 to 20 mg/kg/day (8 to 10 mg/lb/day) divided into three or four equal doses. Clindamycin should be dosed based on total body weight regardless of obesity.

CLEOCIN HCl Capsules are not suitable for pediatric patients who are unable to swallow them whole. The capsules do not provide exact mg/kg doses therefore it may be necessary to use the clindamycin palmitate oral solution in some cases.

Serious infections due to anaerobic bacteria are usually treated with CLEOCIN PHOSPHATE® Sterile Solution. However, in clinically appropriate circumstances, the physician may elect to initiate treatment or continue treatment with CLEOCIN HCl Capsules.

In cases of β-hemolytic streptococcal infections, treatment should continue for at least 10 days.

HOW SUPPLIED

CLEOCIN HCl Capsules are available in the following strengths, colors and sizes:

75 mg Green
 | Bottles of 100 | NDC 0009-0331-02

150 mg Light Blue and Green
 | Bottles of 100 | NDC 0009-0225-02

300 mg Light Blue
 | Bottles of 100 | NDC 0009-0395-14

STORAGE AND HANDLING

Store at controlled room temperature 20° to 25° C (68° to 77° F) [See USP].

Rx only

REFERENCES

1. Smith RB, Phillips JP: Evaluation of CLEOCIN HCl and CLEOCIN Phosphate in an Aged Population. Upjohn TR 8147-82-9122-021, December 1982.

This product's labeling may have been updated. For the most recent prescribing information, please visit www.pfizer.com.

LAB-0040-30.0
Revised: 10/2025

PRINCIPAL DISPLAY PANEL - 75 mg Capsule Bottle Label

Pfizer
NDC 0009-0331-02

Cleocin HCl®

clindamycin hydrochloride
capsules, USP

75 mg*

100 Capsules
Rx only

PRINCIPAL DISPLAY PANEL - 150 mg Capsule Bottle Label

Pfizer
NDC 0009-0225-02

Cleocin HCl®

clindamycin hydrochloride
capsules, USP

150 mg*

100 Capsules
Rx only

PRINCIPAL DISPLAY PANEL - 300 mg Capsule Bottle Label

Pfizer
NDC 0009-0395-14

Cleocin HCl®

clindamycin hydrochloride
capsules, USP

300 mg*

100 Capsules
Rx only